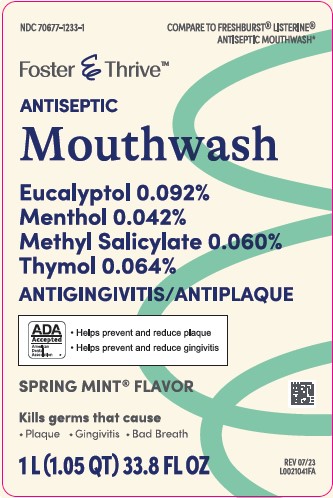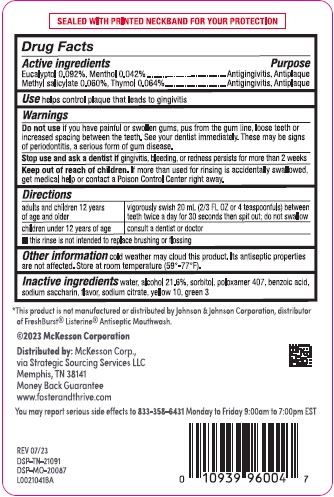 DRUG LABEL: Eucalyptol, Menthol, Methyl salicylate, Thymol
NDC: 70677-1233 | Form: MOUTHWASH
Manufacturer: Strategic Sourcing Services LLC
Category: otc | Type: HUMAN OTC DRUG LABEL
Date: 20260217

ACTIVE INGREDIENTS: EUCALYPTOL 0.92 mg/1 mL; MENTHOL, UNSPECIFIED FORM 0.42 mg/1 mL; METHYL SALICYLATE 0.6 mg/1 mL; THYMOL 0.64 mg/1 mL
INACTIVE INGREDIENTS: WATER; ALCOHOL; SORBITOL; POLOXAMER 407; BENZOIC ACID; SACCHARIN SODIUM; SODIUM CITRATE, UNSPECIFIED FORM; D&C YELLOW NO. 10; FD&C GREEN NO. 3

Foster & Thrive 072.003/072AL rev2 - AN
Spring Mint Antiseptic Mouthrinse

Tamper Evident Statement

Sealed With Printed Neckband For Your Protection

Active ingredients

Eucalyptol 0.092%

Menthol 0.042%

Methyl salicylate 0.060%

Thymol 0.064%

Purpose

Antigingivitis, Antiplaque

Use

helps control plaque that leads to gingivitis

Warnings

for this product

Do not use

if you have painful or swollen gums, pus from the gum line, loose teeth or increased spacing between the teeth. See your dentist immediately. These may be signs of periodontitis, a serious form of gum disease.

Stop use and ask a dentist if

gingivitis, bleeding, or redness persists for more than 2 weeks

Keep out of reach of children.

If more than used for rinsing is accidentally swallowed, get medical help or contact a Poison Control Center right away.

Directions

adults and children 12 years of age and older - vigorously swish 20 mL (2/3 FL OZ or 4 teaspoonfuls) between teeth twice a day for 30 seconds then spit out; do not swallow

children under 12 years of age - consult a dentist or doctor

- this rinse is not intended to replace brushing or flossing

Other information

cold weather may cloud this product. Its antiseptic properties are not affected. Store at room temperature (59°-77°F).

Inactive ingredients

water, alcohol 21.6%, sorbitol, poloxamer 407, benzoic acid, sodium saccharin, flavor, sodium citrate, yellow 10, green 3

Disclaimer

*This product is not manufactured or distributed by Johnson & Johnson Corporation, distributor of FreshBurst®Listerine®Antiseptic Mouthwash.

Adverse Reactions

©2023 McKesson Corporation

Distributed by: McKesson Corp.

Via Strategic Sourcing Services LLC

Memphis, TN 38141

Mone Back Guarantee

www.fosterandthrive.com

You may report serious side effects to 833-358-6431 Monday to Friday 9:00am to 7:00pm EST

REV 07/23

DSP-TN-21091

DSP-MO-20087

Principal display panel

NDC 70677-1233-1

COMPARE TO FRESHBURST®LISTERINE®ANTISEPTIC MOUTHWASH*

Foster & Thrive™

Antiseptic Mouthwash

Eucalyptol 0.092%

Menthol 0.042%

Methyl Salicylate 0.060%

Thymol 0.064%

ANTIGINGIVITIS/ANTIPLAQUE

ADA Accepted

American Dental Association

- Helps prevent and reduce plaque
- Helps prevent and reduce gingivitis

SPRING MINT®FLAVOR

Kills germs that cause

- plaque
- gingivitis
- bad breath

1 L (1.05 QT) 33.8 FL OZ